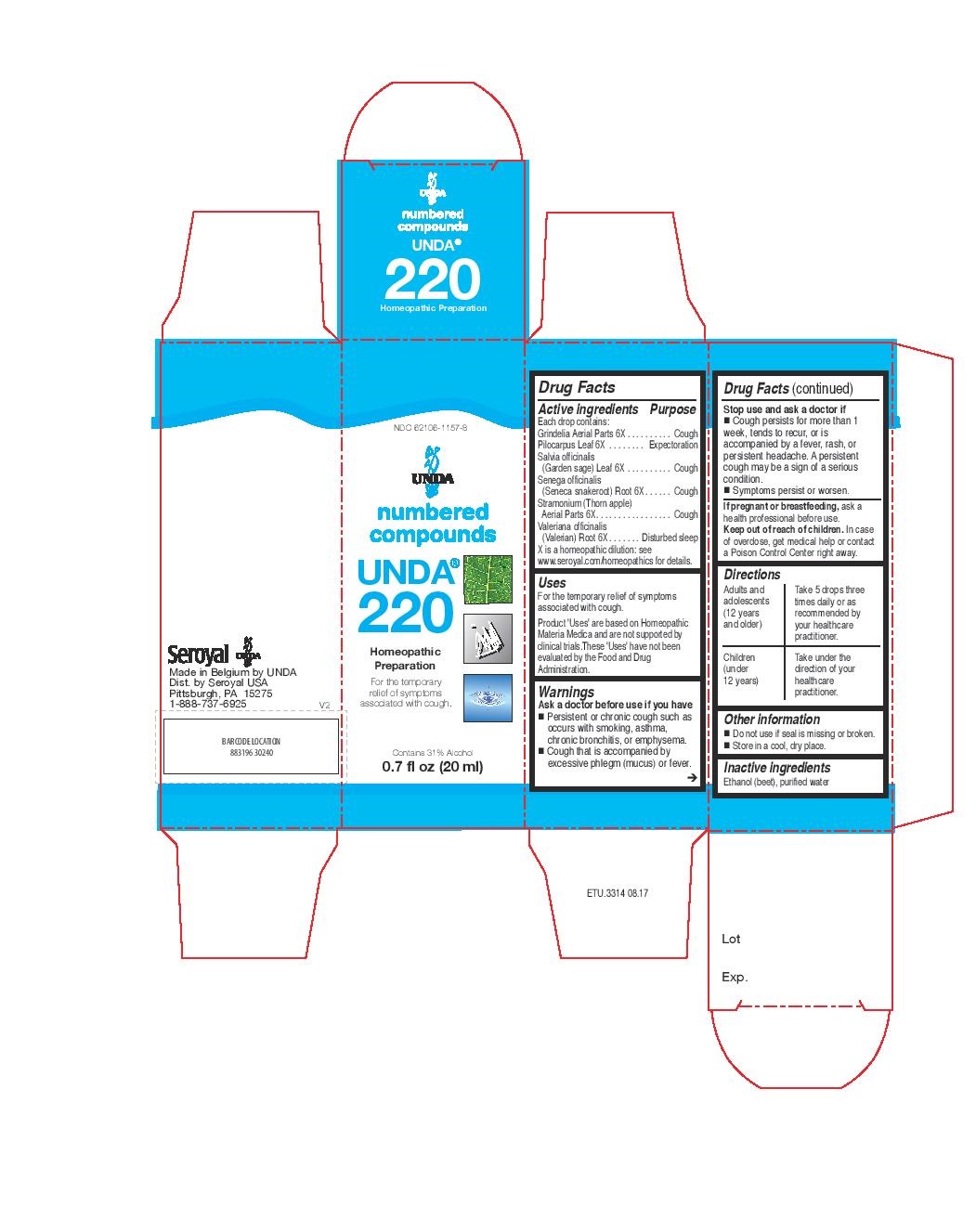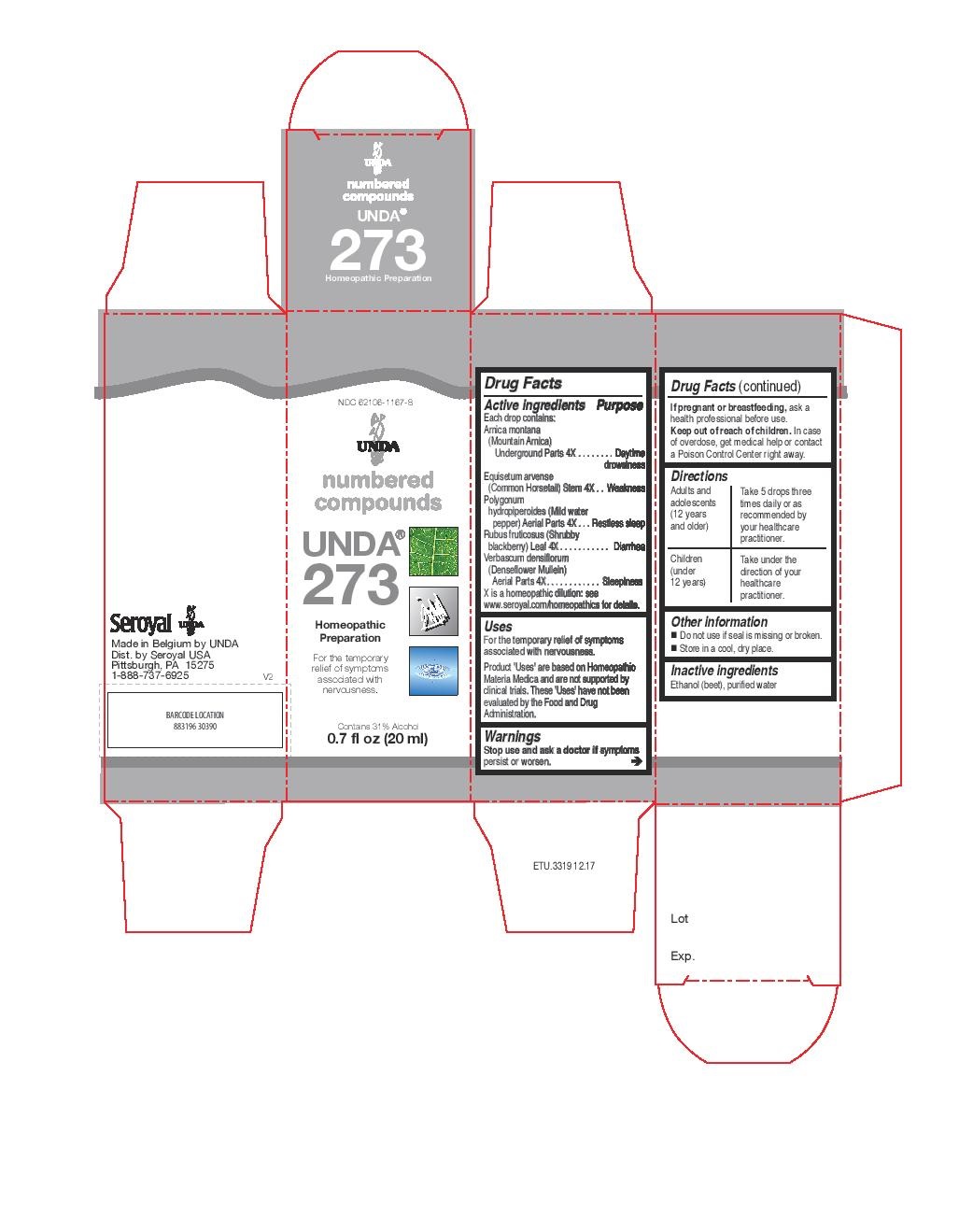 DRUG LABEL: UNDA 220
NDC: 62106-1157 | Form: LIQUID
Manufacturer: Seroyal USA
Category: homeopathic | Type: HUMAN OTC DRUG LABEL
Date: 20221109

ACTIVE INGREDIENTS: GRINDELIA HIRSUTULA FLOWERING TOP 6 [hp_X]/20 mL; PILOCARPUS MICROPHYLLUS LEAF 6 [hp_X]/20 mL; SAGE 6 [hp_X]/20 mL; DATURA STRAMONIUM 6 [hp_X]/20 mL; VALERIAN 6 [hp_X]/20 mL; POLYGALA SENEGA ROOT 6 [hp_X]/20 mL
INACTIVE INGREDIENTS: WATER; ALCOHOL

UNDA 220 and 273

Active ingredients

Each drop contains:

Grindelia Aerial Parts 6X
Pilocarpus Leaf 6X
Salvia officinalis (Garden sage) Leaf 6X
Senega officinalis Root 6X
Stramonium (Thorn apple) Aerial Parts 6X
Valeriana officinalis (Valerian) Root 6X

Uses
For the temporary relief of symptoms associated with cough.

Warnings
Ask a doctor before use if you have

Persistent or chronic cough such as occurs with smoking, asthma, chronic bronchitis, or emphysema.

Cough that is accompanied by excessive phlegm (mucus) or fever.

Stop use and ask a doctor if
Cough persists for more than 1 week, tends to recur, or is accompanied by a fever, rash, or
persistent headache. A persistent cough may be a sign of a serious condition.
Symptoms persist or worsen.

If pregnant or breastfeeding, ask a health professional before use.
Keep out of reach of children. In case of overdose, get medical help or contact
a Poison Control Center right away.

Stop use and ask a doctor if
Cough persists for more than 1 week, tends to recur, or is accompanied by a fever, rash, or persistent headache. A persistent
cough may be a sign of a serious condition.
Symptoms persist or worsen.

PREGNANCY OR BREAST FEEDING

If pregnant or breastfeeding, ask a health professional before use.

Keep out of reach of children.

OVERDOSAGE

In case of overdose, get medical help or contact a Poison Control Center right away.

Inactive ingredients
Ethanol (beet), purified water

Other information
Do not use if seal is missing or broken.
Store in a cool, dry place.

Directions
Adults and adolescents (12 years and older): Take 5 drops three times daily or as
recommended by your healthcare practitioner.
Children (under 12 years): Take under the direction of your
healthcare practitioner.

Uses

For the temporary relief of symptoms associated with cough.

Directions
Adults and adolescents (12 years and older): Take 5 drops three times daily or as
recommended by your healthcare practitioner.
Children (under 12 years): Take under the direction of your
healthcare practitioner.

Active ingredients

Each drop contains:

Arnica montana (Mountain Arnica) Root 4X
Equisetum arvense (Common Horsetail) Stem 4X
Polygonum hydropiperoides (Mild water pepper) Whole Plant 4X
Rubus fruticosus (Shrubby blackberry) Leaf 4X
Verbascum densiflorum Aerial Parts 4X

Uses

For the temporary relief of symptoms associated with nervousness.

Warnings
Stop use and ask a doctor if symptoms persist or worsen.
If pregnant or breastfeeding, ask a health professional before use.
Keep out of reach of children.
In case of overdose, get medical help or contact a Poison Control Center right away.

Stop use and ask a doctor if symptoms persist or worsen.

PREGNANCY OR BREAST FEEDING

If pregnant or breastfeeding, ask a health professional before use.

Keep out of reach of children.

OVERDOSAGE

In case of overdose, get medical help or contact a Poison Control Center right away.

Inactive ingredients
Ethanol (beet), purified water

Other information
Do not use if seal is missing or broken.
Store in a cool, dry place.

Directions
Adults and adolescents (12 years and older): Take 5 drops three times daily or as
recommended by your healthcare practitioner.
Children (under 12 years): Take under the direction of your
healthcare practitioner.

Uses

For the temporary relief of symptoms associated with nervousness.

Directions
Adults and adolescents (12 years and older): Take 5 drops three times daily or as
recommended by your healthcare practitioner.
Children (under 12 years): Take under the direction of your
healthcare practitioner.

PACKAGE LABEL

NDC 62106-1157-8

UNDA
numbered compounds
UNDA 220
Homeopathic Preparation

For the temporary
relief of symptoms
associated with cough.
Contains 31% Alcohol
0.7 fl oz (20 mL)

PACKAGE LABEL

NDC 62106-1167-8

UNDA
numbered compounds
UNDA 273
Homeopathic Preparation

For the temporary relief of symptoms associated with nervousness.
Contains 31% Alcohol
0.7 fl oz (20 mL)